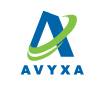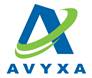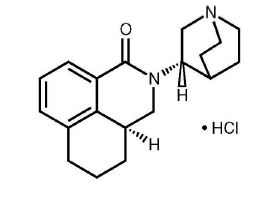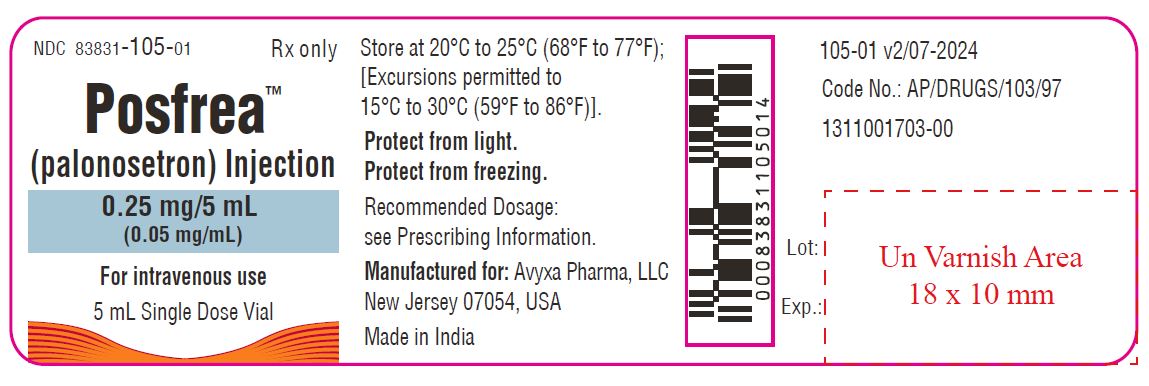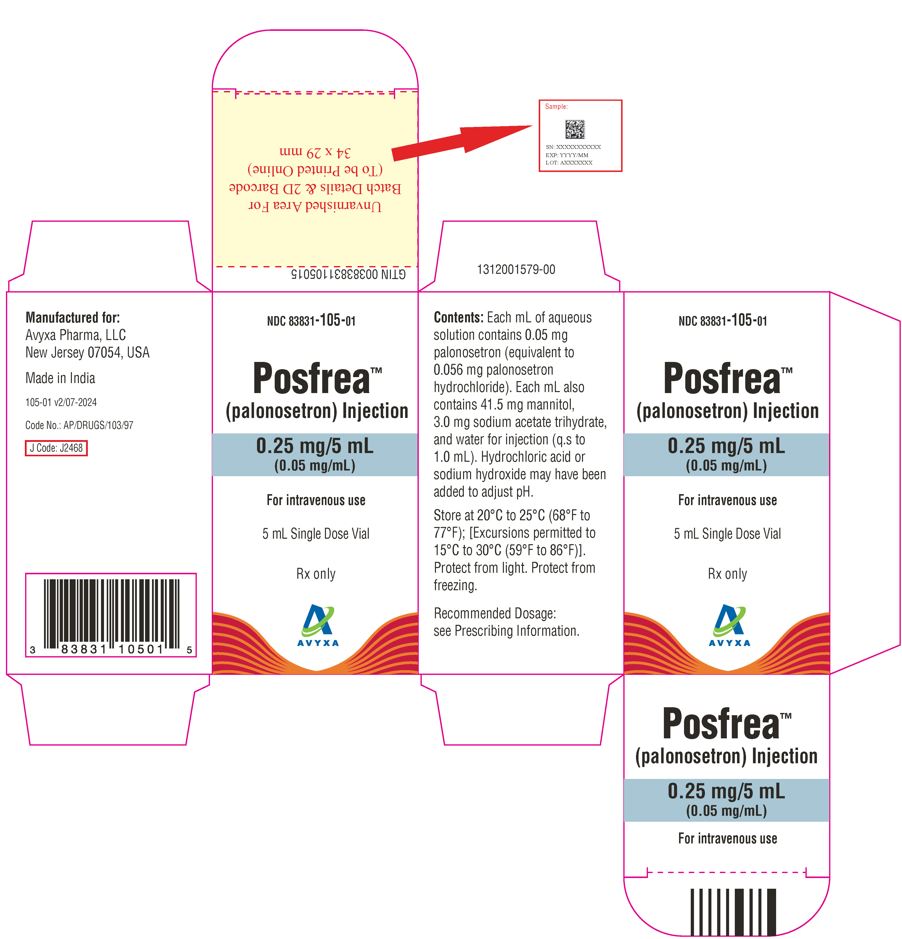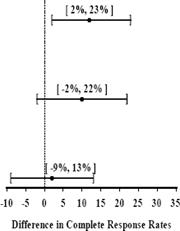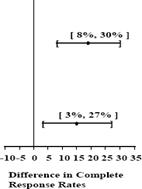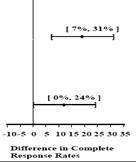 DRUG LABEL: posfrea
NDC: 83831-105 | Form: INJECTION, SOLUTION
Manufacturer: Avyxa Pharma, LLC
Category: prescription | Type: HUMAN PRESCRIPTION DRUG LABEL
Date: 20250429

ACTIVE INGREDIENTS: PALONOSETRON HYDROCHLORIDE 0.25 mg/5 mL
INACTIVE INGREDIENTS: MANNITOL; SODIUM ACETATE; WATER

HIGHLIGHTS OF PRESCRIBING INFORMATION

These highlights do not include all the information needed to use POSFREA safely and effectively. See full prescribing information for POSFREA.
POSFREATM (palonosetron) injection, for intravenous use
Initial U.S. Approval: 2003

RECENT MAJOR CHANGES

Indications and Usage (1) 4/2025

Dosage and Administration (2.1) 4/2025

1 INDICATIONS AND USAGE

POSFREA is a serotonin-3 (5-HT3) receptor antagonist indicated in:

Adults for prevention of:

- acute and delayed nausea and vomiting associated with initial and repeat courses of moderately emetogenic cancer chemotherapy (MEC). (1)
- acute nausea and vomiting associated with initial and repeat courses of highly emetogenic cancer chemotherapy (HEC). (1)
- postoperative nausea and vomiting (PONV) for up to 24 hours following surgery. Efficacy beyond 24 hours has not been demonstrated (1)

Pediatric patients 1 month to less than 17 years of age for prevention of:

- acute nausea and vomiting associated with initial and repeat courses of emetogenic cancer chemotherapy, including highly emetogenic cancer chemotherapy (HEC). (1)

2 DOSAGE AND ADMINISTRATION

Chemotherapy-Induced Nausea and Vomiting (CINV) (2.1)

Age | Dose* | Infusion Time
Adults | 0.25 mg as a single dose | Infuse over 30 seconds beginning approximately 30 minutes before the start of chemotherapy
Pediatrics (1 month to less than 17 years) | 20 micrograms per kilogram (maximum 1.5 mg) as a single dose | Infuse over 15 minutes beginning approximately 30 minutes before the start of chemotherapy
*Note different dosing units in pediatrics

Postoperative Nausea and Vomiting (2.1)

- The recommended adult dosage is 0.075 mg as a single intravenous dose administered over 10 seconds immediately before the induction of anesthesia.

3 DOSAGE FORM AND STRENGTHS

Injection:

- 0.25 mg palonosetron in 5 mL (0.05 mg/mL) in a single-dose vial (3)
- 0.075 mg palonosetron in 1.5 mL (0.05 mg/mL) in a single-dose vial (3)

4 CONTRAINDICATIONS

Hypersensitivity to palonosetron or any of its components. (4)

5 WARNINGS AND PRECAUTIONS

- Hypersensitivity reactions, including anaphylaxis and anaphylactic shock: reported in patients with or without known hypersensitivity to other selective 5-HT3receptor antagonists. If symptoms occur, discontinue POSFREA and initiate appropriate medical treatment. (5.1)
- Serotonin syndrome: reported with 5-HT3receptor antagonists alone, but particularly with concomitant use of serotonergic drugs. (5.2, 7.1)

6 ADVERSE REACTIONS

Most common adverse reactions in

- chemotherapy-induced nausea and vomiting in adults (≥5%) are: headache and constipation (6.1)
- postoperative nausea and vomiting (≥ 2%) are: QT prolongation, bradycardia, headache, and constipation (6.1)

To report SUSPECTED ADVERSE REACTIONS, contact Avyxa Pharma, LLC at 1-888-520-0954 or FDA at 1-800-FDA-1088 or www.fda.gov/medwatch.

7 DRUG INTERACTIONS

Serotonergic Drugs: Monitor for serotonin syndrome; if symptoms occur, discontinue POSFREA and initiate supportive treatment (7.1)

FULL PRESCRIBING INFORMATION

1 INDICATIONS AND USAGE

POSFREA is indicated in adults for prevention of:

- acute and delayed nausea and vomiting associated with initial and repeat courses of moderately emetogenic cancer chemotherapy (MEC).
- acute nausea and vomiting associated with initial and repeat courses highly emetogenic cancer chemotherapy (HEC).
- postoperative nausea and vomiting (PONV) for up to 24 hours following surgery. Efficacy beyond 24 hours has not been demonstrated.

As with other antiemetics, routine prophylaxis is not recommended in patients in whom there is little expectation that nausea and/or vomiting will occur postoperatively. In patients where nausea and vomiting must be avoided during the postoperative period, POSFREA is recommended even where the incidence of postoperative nausea and/or vomiting is low.

POSFREA is indicated in pediatric patients 1 month to less than 17 years of age for prevention of:

- acute nausea and vomiting associated with initial and repeat courses of emetogenic cancer chemotherapy, including highly emetogenic cancer chemotherapy.

2 DOSAGE AND ADMINISTRATION

2.1 Recommended Dosage

Prevention of Chemotherapy-Induced Nausea and Vomiting (CINV)
The recommended dosage of POSFREA for prevention of nausea and vomiting associated with HEC and MEC in adults and associated with emetogenic chemotherapy, including HEC in pediatric patients 1 month to less than 17 years of age is shown in Table 1.

Table 1: Recommended Dosage of POSFREA for the Prevention of Nausea and Vomiting Associated with Chemotherapy in Adults and Pediatric Patients 1 Month to Less than 17 Years
Age | Dose* | Infusion Time
Adults | 0.25 mg as a single dose | Infuse over 30 seconds beginning approximately 30 minutes before the start of chemotherapy
Pediatrics (1 month to less than 17 years) | 20 micrograms per kilogram (max 1.5 mg) as a single dose | Infuse over 15 minutes beginning approximately 30 minutes before the start of chemotherapy
*Note different dosing units in pediatrics

Postoperative Nausea and Vomiting

The recommended dosage of POSFREA in adults for PONV is 0.075 mg administered as a single intravenous dose over 10 seconds immediately before the induction of anesthesia.

2.2 Instructions for Intravenous Administration

- POSFREA is supplied ready for intravenous administration at a concentration of 0.05 mg/mL (50 mcg/mL).
- Do not mix POSFREA with other drugs.
- Flush the infusion line with 0.9% Sodium Chloride Injection before and after administration of POSFREA.
- Inspect POSFREA visually for particulate matter and discoloration before administration.
- Discard unused portion.

3 DOSAGE FORM AND STRENGTHS

POSFREA injection is sterile, clear, and colorless solution in a single-dose vial:

- 0.25 mg palonosetron in 5 mL (0.05 mg/mL)
- 0.075 mg palonosetron in 1.5 mL (0.05 mg/mL)

4 CONTRAINDICATIONS

POSFREA is contraindicated in patients known to have hypersensitivity to palonosetron [see Warnings and Precautions (5.1)].

5 WARNINGS AND PRECAUTIONS

5.1 Hypersensitivity Reactions

Hypersensitivity reactions, including anaphylaxis and anaphylactic shock, have been reported with administration of palonosetron [see Adverse Reactions (6.2)]. These reactions occurred in patients with or without known hypersensitivity to other 5-HT3 receptor antagonists. If hypersensitivity reactions occur, discontinue POSFREA and initiate appropriate medical treatment. Do not reinitiate POSFREA in patients who have previously experienced symptoms of hypersensitivity [see Contraindications (4)].

5.2 Serotonin Syndrome

The development of serotonin syndrome has been reported with 5-HT3 receptor antagonists. Most reports have been associated with concomitant use of serotonergic drugs (e.g., selective serotonin reuptake inhibitors (SSRIs), serotonin and norepinephrine reuptake inhibitors (SNRIs), monoamine oxidase inhibitors, mirtazapine, fentanyl, lithium, tramadol, and intravenous methylene blue). Some of the reported cases were fatal. Serotonin syndrome occurring with overdose of another 5-HT3 receptor antagonist alone has also been reported. The majority of reports of serotonin syndrome related to 5-HT3 receptor antagonist use occurred in a post- anesthesia care unit or an infusion center.

Symptoms associated with serotonin syndrome may include the following combination of signs and symptoms: mental status changes (e.g., agitation, hallucinations, delirium, and coma), autonomic instability (e.g., tachycardia, labile blood pressure, dizziness, diaphoresis, flushing, hyperthermia), neuromuscular symptoms (e.g., tremor, rigidity, myoclonus, hyperreflexia, incoordination), seizures, with or without gastrointestinal symptoms (e.g., nausea, vomiting, diarrhea). Patients should be monitored for the emergence of serotonin syndrome, especially with concomitant use of POSFREA and other serotonergic drugs. If symptoms of serotonin syndrome occur, discontinue POSFREA and initiate supportive treatment. Patients should be informed of the increased risk of serotonin syndrome, especially if POSFREA is used concomitantly with other serotonergic drugs [see Drug Interactions (7.1)].

6 ADVERSE REACTIONS

Serious or otherwise clinically significant adverse reactions reported in other sections of labeling:

- Hypersensitivity Reactions [see Warnings and Precautions (5.1)]
- Serotonin Syndrome [see Warnings and Precautions (5.2)]

6.1 Clinical Trials Experience

Because clinical trials are conducted under widely varying conditions, adverse reaction rates observed in the clinical trials of a drug cannot be directly compared to rates in the clinical trials of another drug and may not reflect the rates observed in practice.

The safety of POSFREA has been established from adequate and well-controlled studies of another intravenous formulation of palonosetron [see Clinical Studies (14)]. Below is a display of the adverse reactions of palonosetron in these adequate and well-controlled studies.

Chemotherapy-Induced Nausea and Vomiting (CINV)

Adults

In double-blind randomized clinical trials for the prevention of nausea and vomiting induced by MEC or HEC, 1374 adult patients received a single dose of palonosetron, ondansetron (Studies 1 and 3) or dolasetron (Study 2) administered intravenously 30 minutes prior to chemotherapy [see Clinical Studies (14.1)]. Adverse reactions were similar in frequency and severity in all three treatment groups. Common adverse reactions reported in at least 2% of patients in these trials are shown in Table 2.

Table 2: Common Adverse Reactions* in Adults with Receiving MEC (Studies 1 and 2) or HEC (Study 3)
Adverse Reaction | Palonosetron 0.25 mg intravenously (N=633) | Ondansetron 32 mg intravenously (N=410) | Dolasetron 100 mg intravenously (N=194)
Headache | 9% | 8% | 16%
Constipation | 5% | 2% | 6%
Diarrhea | 1% | 2% | 2%
Dizziness | 1% | 2% | 2%
Fatigue | < 1% | 1% | 2%
Abdominal Pain | < 1% | < 1% | 2%
Insomnia | < 1% | 1% | 2%
*Reported in at least 2% of patients in any treatment group

Less common adverse reactions, reported in 1% or less of patients in any treatment group, in Studies 1, 2 and 3 were:

- Cardiac disorders: non-sustained tachycardia, bradycardia, myocardial ischemia, extrasystoles, sinus tachycardia, sinus arrhythmia, supraventricular extrasystoles.
- Skin & subcutaneous tissue disorders: allergic dermatitis, rash.
- Ear &labyrinth disorders: motion sickness, tinnitus.
- Gastrointestinal disorders: diarrhea, dyspepsia, abdominal pain, dry mouth, hiccups and flatulence.
- General disorders and administration site conditions: weakness, fatigue, fever, hot flash, flu-like syndrome.
- Investigations: QT prolongation, transient, asymptomatic increases in AST and/or ALT and bilirubin and these changes occurred predominantly in patients receiving HEC.
- Metabolism and nutrition disorders: hyperkalemia, electrolyte fluctuations, hyperglycemia, metabolic acidosis, appetite decrease, anorexia.
- Musculoskeletal and connective tissue disorders: arthralgia.
- Nervous System disorders: dizziness, somnolence, insomnia, hypersomnia, paresthesia.
- Psychiatric disorders: anxiety, euphoric mood.
- Renal and urinary disorders: urinary retention, glycosuria.
- Vascular disorders: vein discoloration, vein distention, hypotension, hypertension.

In other studies, two subjects experienced severe constipation following a single dose of approximately 0.75 mg (three times the recommended dose).

Pediatrics Aged 2 Months to 17 Years

In a pediatric clinical trial, 163 pediatric cancer patients with a mean age of eight years received a single 20 mcg/kg (maximum 1.5 mg) intravenous infusion of palonosetron 30 minutes before beginning the first cycle of emetogenic chemotherapy [see Clinical Studies (14.2)]. Adverse reactions were evaluated in pediatric patients receiving palonosetron for up to four chemotherapy cycles. The following adverse reactions were reported in less than 1% of palonosetron-treated patients:

- Nervous System disorders: headache, dizziness, dyskinesia.
- General disorders and administration site conditions: infusion site pain.
- Skin and subcutaneous tissue disorders: allergic dermatitis, skin disorder.

Postoperative Nausea and Vomiting (PONV)

The most common adverse reactions reported in at least 2% of adults receiving palonosetron 0.075 mg intravenously immediately before induction of anesthesia in three randomized placebo-controlled trials [see Clinical Studies (14.3)] are shown in Table 3. Rates of adverse reactions between palonosetron and placebo groups were similar. Some events are known to be associated with, or may be exacerbated by, concomitant perioperative and intraoperative medications administered in this surgical population. A thorough QT/QTc study demonstrated palonosetron does not prolong the QT interval to any clinically relevant extent [see Clinical Pharmacology (12.2)].

Table 3: Common Adverse Reactions* in Trials of Adults with Postoperative Nausea and Vomiting
Adverse Reaction | Palonosetron 0.075 mg intravenously (N=336) | Placebo (N=369)
Electrocardiogram QT prolongation | 5% | 3%
Bradycardia | 4% | 4%
Headache | 3% | 4%
Constipation | 2% | 3%
*Reported in at least 2% of patients in any treatment group

Less common adverse reactions, reported in 1% or less of patients, in these PONV clinical trials were:

- Cardiac disorders: sinus bradycardia, tachycardia, arrhythmia, ventricular extrasystoles. The frequency of these adverse effects did not appear to be different from placebo.
- Skin and subcutaneous tissue disorders: pruritus.
- Gastrointestinal disorders: flatulence, dry mouth, upper abdominal pain, salivary hypersecretion, dyspepsia, diarrhea, intestinal hypomotility.
- General disorders and administration site conditions: chills, generalized edema.
- Investigations: increases in AST and/or ALT, hepatic enzyme increased, QTc prolongation, blood pressure decreased, platelet count decreased, T wave amplitude decreased.
- Metabolism and nutrition disorders: hypokalemia, anorexia.
- Nervous System disorders: dizziness.
- Respiratory, thoracic and mediastinal disorders: hypoventilation, laryngospasm.
- Renal and urinary disorders: Urinary retention.
- Vascular disorders: Hypotension, Hypertension.

6.2 Postmarketing Experience

The following adverse reactions have been identified during postapproval use of palonosetron. Because these reactions are reported voluntarily from a population of uncertain size, it is not always possible to reliably estimate their frequency or establish a causal relationship to drug exposure.

- Hypersensitivity reactions: including dyspnea, bronchospasm, swelling/edema, erythema, pruritus, rash, urticaria, anaphylaxis and anaphylactic shock [see Warnings and Precautions (5.1)]
- Injection site reactions: including burning, induration, discomfort and pain

7 DRUG INTERACTIONS

7.1 Serotonergic Drugs

Serotonin syndrome (including altered mental status, autonomic instability, and neuromuscular symptoms) has been described following the concomitant use of 5-HT3 receptor antagonists and other serotonergic drugs, including selective serotonin reuptake inhibitors (SSRIs) and serotonin and noradrenaline reuptake inhibitors (SNRIs). Monitor for the emergence of serotonin syndrome. If symptoms occur, discontinue POSFREA and initiate supportive treatment [see Warnings and Precautions (5.2)].

8 USE IN SPECIFIC POPULATIONS

8.1 Pregnancy

Risk Summary

There are no available data on palonosetron use in pregnant women to inform a drug-associated risk.

In animal reproduction studies, no effects on embryo-fetal development were observed with the administration of oral palonosetron during the period of organogenesis at doses up to 1,894 and 3,789 times the recommended human intravenous dose in rats and rabbits, respectively (see Data).

The background risk of major birth defects and miscarriage for the indicated population is unknown. All pregnancies have a background risk of birth defect, loss, or other adverse outcomes. In the U.S. general population, the estimated background risk of major birth defects and miscarriage in clinically recognized pregnancies is 2 to 4% and 15 to 20%, respectively.

Data

Animal Data

In animal reproduction studies, no effects on embryo-fetal development were observed in pregnant rats given oral palonosetron at doses up to 60 mg/kg/day (1,894 times the recommended human intravenous dose based on body surface area) or pregnant rabbits given oral doses up to 60 mg/kg/day (3,789 times the recommended human intravenous dose based on body surface area) during the period of organogenesis.

8.2 Lactation

Risk Summary

There are no data on the presence of palonosetron in human milk, the effects of palonosetron on the breastfed infant, or the effects of palonosetron on milk production. The developmental and health benefits of breastfeeding should be considered along with the mother's clinical need for POSFREA and any potential adverse effect on the breastfed infant from palonosetron or from the underlying maternal condition.

8.4 Pediatric Use

Chemotherapy-Induced Nausea and Vomiting (CINV)

Safety and effectiveness of POSFREA have been established in pediatric patients aged 1 month to less than 17 years for the prevention of acute nausea and vomiting associated with initial and repeat courses of emetogenic cancer chemotherapy, including HEC. Use is supported by a clinical trial where 165 pediatric patients aged two months to less than 17 years were randomized to receive a single dose of palonosetron 20 mcg/kg (maximum 1.5 mg) administered as an intravenous infusion 30 minutes prior to the start of emetogenic chemotherapy [see Clinical Studies (14.2)]. While this study demonstrated that pediatric patients require a higher palonosetron dose than adults to prevent chemotherapy-induced nausea and vomiting, the safety profile is consistent with the established profile in adults [see Adverse Reactions (6.1)].

Safety and effectiveness of POSFREA in neonates (less than 1 month of age) have not been established.

Postoperative Nausea and Vomiting Studies (PONV)

Safety and effectiveness have not been established in pediatric patients for PONV. Two pediatric trials were performed.

Pediatric Study 1, a dose finding study was conducted to compare two doses of palonosetron, 1 mcg/kg (maximum 0.075 mg) versus 3 mcg/kg (maximum 0.25 mg). A total of 150 pediatric surgical patients participated, age range one month to less than 17 years. No dose response was observed.

Pediatric Study 2, a multicenter, double-blind, double-dummy, randomized, parallel group, active control, single-dose non-inferiority study, compared intravenous palonosetron (1 mcg/kg, maximum 0.075 mg) versus intravenous ondansetron. A total of 670 pediatric surgical patients participated, age 30 days to less than 17 years. The primary efficacy endpoint, Complete Response (CR: no vomiting, no retching, and no antiemetic rescue medication) during the first 24 hours postoperatively was achieved in 78.2% of patients in the palonosetron group and 82.7% in the ondansetron group. Given the pre-specified non-inferiority margin of -10%, the stratum adjusted Mantel-Haenszel statistical non-inferiority confidence interval for the difference in the primary endpoint, complete response (CR), was [-10.5, 1.7%], therefore non-inferiority was not demonstrated. Adverse reactions to palonosetron were similar to those reported in adults.

8.5 Geriatric Use

Of the 1374 adult cancer patients in clinical studies of intravenously administered palonosetron for CINV, 316 (23%) were 65 years and over, while 71 (5%) were at least 75 years and over. Of the 1520 adult patients in clinical studies of intravenously administered palonosetron for PONV, 73 (5%) were at least 65 years old [see Clinical Studies (14.1, 14.3)]. No overall differences in safety or effectiveness were observed between these subjects and younger subjects, but greater sensitivity in some older individuals cannot be ruled out. Population pharmacokinetics analysis did not reveal any differences in palonosetron pharmacokinetics between cancer patients 65 years of age and older compared to younger patients [see Clinical Pharmacology (12.3)]. No dosage adjustment is required for geriatric patients.

10 OVERDOSAGE

There is no known antidote to palonosetron. Overdose should be managed with supportive care.

Dialysis studies have not been performed, however, due to the large volume of distribution, dialysis is unlikely to be an effective treatment for palonosetron overdose. A single intravenous dose of palonosetron at 30 mg/kg (947 and 474 times the human dose for rats and mice, respectively, based on body surface area) was lethal to rats and mice. The major signs of toxicity were convulsions, gasping, pallor, cyanosis and collapse.

11 DESCRIPTION

POSFREA Injection contains palonosetron as palonosetron HCl, an antiemetic and antinauseant agent. It is a serotonin-3 (5-HT3) receptor antagonist with a strong binding affinity for this receptor. Chemically, palonosetron HCl is: (3aS)-2-[(S)-1-Azabicyclo [2.2.2]oct 3-yl]-2,3,3a,4,5,6-hexahydro-1-oxo-1Hbenz[de]isoquinoline hydrochloride. The empirical formula is C19H24N2O.HCl, with a molecular weight of 332.87. Palonosetron HCl exists as a single isomer and has the following structural formula:

Palonosetron HCl is a white to off-white crystalline powder. It is freely soluble in water, soluble in propylene glycol, and slightly soluble in ethanol and 2-propanol.

POSFREA Injection is a sterile, clear, colorless, non-pyrogenic, isotonic, buffered solution for intravenous administration. POSFREA Injection is available as a 5 mL or 1.5 mL single-dose vial.

Each mL of aqueous solution contains 0.05 mg palonosetron (equivalent to 0.056 mg palonosetron hydrochloride). Each mL also contains 41.5 mg mannitol, 3.0 mg sodium acetate trihydrate, and water for injection (q.s. to 1.0 mL).

The pH of the solution in the 5 mL and 1.5 mL vials is 4.5 to 5.5. Hydrochloric acid or sodium hydroxide may have been added to adjust pH.

12 CLINICAL PHARMACOLOGY

12.1 Mechanism of Action

Palonosetron is a 5-HT3 receptor antagonist with a strong binding affinity for this receptor and little or no affinity for other receptors.

Cancer chemotherapy may be associated with a high incidence of nausea and vomiting, particularly when certain agents, such as cisplatin, are used. 5-HT3 receptors are located on the nerve terminals of the vagus in the periphery and centrally in the chemoreceptor trigger zone of the area postrema. It is thought that chemotherapeutic agents produce nausea and vomiting by releasing serotonin from the enterochromaffin cells of the small intestine and that the released serotonin then activates 5-HT3 receptors located on vagal afferents to initiate the vomiting reflex.

Postoperative nausea and vomiting is influenced by multiple patient, surgical and anesthesia related factors and is triggered by release of 5-HT in a cascade of neuronal events involving both the central nervous system and the gastrointestinal tract. The 5-HT3 receptor has been demonstrated to selectively participate in the emetic response.

12.2 Pharmacodynamics

Cardiac Electrophysiology

The effect of intravenous palonosetron on blood pressure, heart rate, and ECG parameters including QTc were comparable to intravenous ondansetron and dolasetron in CINV clinical trials. In PONV clinical trials the effect of palonosetron on the QTc interval was no different from placebo. In non-clinical studies palonosetron possesses the ability to block ion channels involved in ventricular de- and re-polarization and to prolong action potential duration.

At a dose of 9 times the maximum recommended adult dose, POSFREA does not prolong the QT interval to any clinically relevant extent.

12.3 Pharmacokinetics

After intravenous dosing of palonosetron in healthy subjects and cancer patients, an initial decline in palonosetron plasma concentrations is followed by a slow elimination from the body. Mean maximum plasma concentration (Cmax) and area under the concentration-time curve (AUC0-∞) are generally dose proportional over the dose range of 0.3 to 90 mcg/kg in healthy subjects and in cancer patients. Following a single intravenous dose of palonosetron at 3 mcg/kg (or 0.21 mg/70 kg) to six cancer patients, mean (±SD) maximum plasma concentration was estimated to be 5630 ± 5480 ng/L and mean AUC was 35.8 ± 20.9 h•mcg/L.

Following intravenous administration of palonosetron 0.25 mg once every other day for 3 doses in 11 cancer patients, the mean increase in plasma palonosetron concentration from Day 1 to Day 5 was 42±34%. Following intravenous administration of palonosetron 0.25 mg once daily for three days in 12 healthy subjects, the mean (±SD) increase in plasma palonosetron concentration from Day 1 to Day 3 was 110±45%.

After intravenous dosing of palonosetron in patients undergoing surgery (abdominal surgery or vaginal hysterectomy), the pharmacokinetic characteristics of palonosetron were similar to those observed in cancer patients.

Distribution

Palonosetron has a volume of distribution of approximately 8.3 ± 2.5 L/kg. Approximately 62% of palonosetron is bound to plasma proteins.

Elimination

After a single intravenous dose of 10 mcg/kg [^14C]-palonosetron, approximately 80% of the dose was recovered within 144 hours in the urine with palonosetron representing approximately 40% of the administered dose. In healthy subjects, the total body clearance of palonosetron was 0.160 ± 0.035 L/h/kg and renal clearance was 0.067± 0.018 L/h/kg. Mean terminal elimination half-life is approximately 40 hours.

Metabolism

Palonosetron is eliminated by multiple routes with approximately 50% metabolized to form two primary metabolites: N-oxide-palonosetron and 6-S-hydroxy-palonosetron. These metabolites each have less than 1% of the 5-HT3 receptor antagonist activity of palonosetron. In vitro metabolism studies have suggested that CYP2D6 and to a lesser extent, CYP3A4 and CYP1A2 are involved in the metabolism of palonosetron. However, clinical pharmacokinetic parameters are not significantly different between poor and extensive metabolizers of CYP2D6 substrates.

Specific Populations

Pediatric Patients

Pharmacokinetic data was obtained from a subset of pediatric cancer patients that received 10 mcg/kg or 20 mcg/kg as a single intravenous dose of palonosetron. When the dose was increased from 10 mcg/kg to 20 mcg/kg a dose-proportional increase in mean AUC was observed. Peak plasma concentrations (CT) reported at the end of the 15-minute infusion of 20 mcg/kg were highly variable in all age groups and tended to be lower in patients less than six years than in older patients as shown in Table 4. The median half-life was 30 hours in overall age groups and ranged from about 20 to 30 hours across age groups after administration of 20 mcg/kg.

The total body clearance (L/h/kg) in patients 12 to 17 years old was similar to that in healthy adults. There are no apparent differences in volume of distribution when expressed as L/kg.

Table 4: Pharmacokinetics Parameters in Pediatric Cancer Patients following Intravenous Infusion of 20 mcg/kg Palonosetron Over 15 minutes
PK Parametera | Pediatric Age Group
PK Parametera | Less than 2 years | 2 years to less than 6 years | 6 years to less than 12 years | 12 years to less than 17 years
 | N=12 | N=42 | N=38 | N=44
CTb, ng/L | 9025 (197) | 9414 (252) | 16275 (203) | 11831 (176)
 |  | N=5 | N=7 | N=10
AUC 0-∞, h·mcg/L |  | 103.5 (40.4) | 98.7 (47.7) | 124.5 (19.1)
 | N=6 | N=14 | N=13 | N=19
Clearance c, L/h/kg | 0.31 (34.7) | 0.23 (51.3) | 0.19 (46.8) | 0.16 (27.8)
VssC, L/kg | 6.08 (36.5) | 5.29 (57.8) | 6.26 (40.0) | 6.20 (29.0)
a Geometric Mean (CV) except for t1/2 which is median values
b CT is the plasma palonosetron concentration at the end of the 15-minute infusion
c Clearance and Vss calculated from 10 and 20 mcg/kg and are weight adjusted

Racial or Ethnic Groups

The pharmacokinetics of palonosetron were characterized in 24 healthy Japanese subjects over an intravenous dose range of 3 to 90 mcg/kg. Total body clearance was 25% higher in Japanese subjects compared to Whites, however, this increase is not considered to be clinically meaningful.

Patients with Renal Impairment

Mild to moderate renal impairment does not significantly affect palonosetron pharmacokinetic parameters. Total systemic exposure increased by approximately 28% in patients with severe renal impairment relative to healthy subjects. This increase is not considered clinically meaningful.

Patients with Hepatic Impairment

Hepatic impairment does not significantly affect total body clearance of palonosetron compared to the healthy subjects.

Drug Interaction Studies

In vitro studies indicated that palonosetron is not an inhibitor of CYP1A2, CYP2A6, CYP2B6, CYP2C9, CYP2D6, CYP2E1 and CYP3A4/5 (CYP2C19 was not investigated) nor does it induce the activity of CYP1A2, CYP2D6, or CYP3A4/5. Therefore, the potential for clinically significant drug interactions with palonosetron appears to be low.

Dexamethasone

Coadministration of 0.25 mg palonosetron and 20 mg dexamethasone administered intravenously in healthy subjects revealed no pharmacokinetic drug-interactions between palonosetron and dexamethasone.

Oral Aprepitant

In an interaction study in healthy subjects where a single 0.25 mg intravenous dose of palonosetron was administered on day 1 and oral aprepitant for three days (125 mg/80 mg/80 mg), the pharmacokinetics of palonosetron were not significantly altered (AUC: no change, Cmax: 15% increase).

Metoclopramide

A study in healthy subjects involving a single 0.75 mg intravenous dose of palonosetron and steady state oral metoclopramide (10 mg four times daily) demonstrated no significant pharmacokinetic interaction.

Corticosteroids, Analgesics, Antiemetics/Antinauseants, Antispasmodics and Anticholinergic Agents

In controlled clinical trials, palonosetron has been safely administered with corticosteroids, analgesics, antiemetics/antinauseants, antispasmodics and anticholinergic agents.

13 NONCLINICAL TOXICOLOGY

13.1 Carcinogenesis, Mutagenesis, Impairment of Fertility

In a 104-week carcinogenicity study in CD-1 mice, animals were treated with oral doses of palonosetron at 10, 30 and 60 mg/kg/day. Treatment with palonosetron was not tumorigenic. The highest tested dose produced a systemic exposure to palonosetron (plasma AUC) of about 150 to 289 times the human exposure (AUC= 29.8 h•mcg/L) at the recommended intravenous dose of 0.25 mg. In a 104-week carcinogenicity study in Sprague-Dawley rats, male and female rats were treated with oral doses of 15, 30 and 60 mg/kg/day and 15, 45 and 90 mg/kg/day, respectively. The highest doses produced a systemic exposure to palonosetron (plasma AUC) of 137 and 308 times the human exposure at the recommended dose. Treatment with palonosetron produced increased incidences of adrenal benign pheochromocytoma and combined benign and malignant pheochromocytoma, increased incidences of pancreatic Islet cell adenoma and combined adenoma and carcinoma and pituitary adenoma in male rats. In female rats, it produced hepatocellular adenoma and carcinoma and increased the incidences of thyroid C-cell adenoma and combined adenoma and carcinoma.

Palonosetron was not genotoxic in the Ames test, the Chinese hamster ovarian cell (CHO/HGPRT) forward mutation test, the ex vivo hepatocyte unscheduled DNA synthesis (UDS) test or the mouse micronucleus test. It was, however, positive for clastogenic effects in the Chinese hamster ovarian (CHO) cell chromosomal aberration test.

Palonosetron at oral doses up to 60 mg/kg/day (about 1894 times the recommended human intravenous dose based on body surface area) was found to have no effect on fertility and reproductive performance of male and female rats.

14 CLINICAL STUDIES

The safety and efficacy of POSFREA have been established based on adequate and well-controlled adult studies of another intravenous formulation of palonosetron in CINV and PONV. Below is a display of the results of these adequate and well-controlled studies of palonosetron in these conditions.

14.1 Prevention of Nausea and Vomiting Associated with MEC and HEC in Adults

Efficacy of a single intravenous dose of palonosetron in preventing acute and delayed nausea and vomiting associated with MEC or HEC were studied in four trials. In these double-blind studies, complete response rates (no emetic episodes and no rescue medication) and other efficacy parameters were assessed through at least 120 hours after administration of chemotherapy. The safety and efficacy of palonosetron in repeated courses of chemotherapy was also assessed.

Moderately Emetogenic Chemotherapy

Two double-blind trials (Study 1 and Study 2) involving 1132 patients compared a single dose of palonosetron with either a single-dose of ondansetron (Study 1) or dolasetron (Study 2) given 30 minutes prior to MEC, including carboplatin, cisplatin ≤ 50 mg/m^2, cyclophosphamide <1500 mg/m^2, doxorubicin > 25 mg/m^2, epirubicin, irinotecan, and methotrexate >250 mg/m^2. Concomitant corticosteroids were not administered prophylactically in Study 1 and were only used by 4 to 6% of patients in Study 2. The majority of patients in these studies were women (77%), White (65%) and naïve to previous chemotherapy (54%). The mean age was 55 years.

Highly Emetogenic Chemotherapy

A double-blind, dose-ranging trial evaluated the efficacy of a single intravenous dose of palonosetron from 0.3 to 90 mcg/kg (equivalent to < 0.1 mg to 6 mg fixed dose) in 161 chemotherapy-naïve adult cancer patients receiving HEC, either cisplatin ≥ 70 mg/m^2 or cyclophosphamide > 1100 mg/m^2. Concomitant corticosteroids were not administered prophylactically. Analysis of data from this trial indicates that 0.25 mg is the lowest effective dose in preventing acute nausea and vomiting associated with HEC.

A double-blind trial involving 667 patients compared a single intravenous dose of palonosetron with a single intravenous dose of ondansetron (Study 3) given 30 minutes prior to HEC, including cisplatin ≥ 60 mg/m^2, cyclophosphamide > 1500 mg/m^2, and dacarbazine. Corticosteroids were co-administered prophylactically before chemotherapy in 67% of patients. Of the 667 patients, 51% were women, 60% White, and 59% naïve to previous chemotherapy. The mean age was 52 years.

Efficacy Results

Studies 1, 2 and 3 show that palonosetron was effective in the prevention of nausea and vomiting associated with initial and repeat courses of MEC and HEC in the acute phase (0 to 24 hours) [Table 5]. Clinical superiority over other 5-HT3 receptor antagonists has not been adequately demonstrated in the acute phase. In Study 3, efficacy was greater when prophylactic corticosteroids were administered concomitantly.

Studies 1 and 2 show that palonosetron was effective in the prevention of nausea and vomiting associated with initial and repeat course of MEC in the delayed phase (24 to 120 hours) [Table 6] and overall phase (0 to 120 hours) [Table 7].

Table 5: Prevention of Acute Nausea and Vomiting (0 to 24 Hours) in Adults with Nausea and Vomiting Associated with MEC or HEC in Studies 1, 2 and 3: Complete Response Rates
Chemotherapy | Study | Treatment Group | Na | % with Complete Response | p-value b | 97.5% Confidence Interval Palonosetron minus Comparator c
Moderately Emetogenic | 1 | Palonosetron 0.25 mg intravenously | 189 | 81 | 0.009 | 97.5% Confidence Interval Palonosetron minus Comparator c
Moderately Emetogenic | 1 | Ondansetron 32 mg intravenouslyd | 185 | 69 | 0.009 | 97.5% Confidence Interval Palonosetron minus Comparator c
Moderately Emetogenic | 2 | Palonosetron 0.25 mg intravenously | 189 | 63 | NS | 97.5% Confidence Interval Palonosetron minus Comparator c
Moderately Emetogenic | 2 | Dolasetron 100 mg intravenously | 191 | 53 | NS | 97.5% Confidence Interval Palonosetron minus Comparator c
Highly Emetogenic | 3 | Palonosetron 0.25 mg intravenously | 223 | 59 | NS | 97.5% Confidence Interval Palonosetron minus Comparator c
Highly Emetogenic | 3 | Ondansetron 32 mg intravenouslyd | 221 | 57 | NS | 97.5% Confidence Interval Palonosetron minus Comparator c
aIntent-to-treat cohort
b2-sided Fisher's exact test. Significance level at α=0.025.
cThese studies were designed to show non-inferiority. A lower bound greater than –15% demonstrates non-inferiority between palonosteron and comparator.
dOndansetron 32 mg intravenously was used in the clinical trial. Although this dose was used in the trial, it is no longer the currently recommended dose. Refer to the ondansetron prescribing information for the current recommended dose.

Table 6: Prevention of Delayed Nausea and Vomiting (24 to 120 Hours) Associated with MEC in Adults in Studies 1 and 2: Complete Response Rates
Chemotherapy | Study | Treatment Group | Na | % with Complete Response | p-value b | 97.5% Confidence Interval Palonosetron minus Comparatorc
Moderately Emetogenic | 1 | Palonosetron 0.25 mg intravenously | 189 | 74 | <0.001 | 97.5% Confidence Interval Palonosetron minus Comparatorc
Moderately Emetogenic | 1 | Ondansetron 32 mg intravenouslyd | 185 | 55 | <0.001 | 97.5% Confidence Interval Palonosetron minus Comparatorc
Moderately Emetogenic | 2 | Palonosetron 0.25 mg intravenously | 189 | 54 | 0.004 | 97.5% Confidence Interval Palonosetron minus Comparatorc
Moderately Emetogenic | 2 | Dolasetron 100 mg intravenously | 191 | 39 | 0.004 | 97.5% Confidence Interval Palonosetron minus Comparatorc
aIntent-to-treat cohort
b2-sided Fisher's exact test. Significance level at α=0.025.
cThese studies were designed to show non-inferiority. A lower bound greater than–15% demonstrates non-inferiority between palonosetron and comparator.
dOndansetron 32 mg intravenously was used in the clinical trial. Although this dose was used in the trial, it is no longer the currently recommended dose. Refer to the ondansetron prescribing information for the current recommended dose.

Table 7: Prevention of Overall Nausea and Vomiting (0 to 120 Hours) Associated with MEC in Adults in Studies 1 and 2: Complete Response Rates
Chemotherapy | Study | Treatment Group | Na | % with Complete Response | p-value b | 97.5% Confidence Interval Palonosetron minus Comparator c
Moderately Emetogenic | 1 | Palonosetron 0.25 mg intravenously | 189 | 69 | <0.001 | 97.5% Confidence Interval Palonosetron minus Comparator c
Moderately Emetogenic | 1 | Ondansetron 32 mg intravenouslyd | 185 | 50 | <0.001 | 97.5% Confidence Interval Palonosetron minus Comparator c
Moderately Emetogenic | 2 | Palonosetron 0.25 mg intravenously | 189 | 46 | 0.021 | 97.5% Confidence Interval Palonosetron minus Comparator c
Moderately Emetogenic | 2 | Dolasetron 100 mg intravenously | 191 | 34 | 0.021 | 97.5% Confidence Interval Palonosetron minus Comparator c
a Intent-to-treat cohort
b 2-sided Fisher's exact test. Significance level at α=0.025.
c These studies were designed to show non-inferiority. A lower bound greater than –15% demonstrates non-inferiority between palonosetron and comparator.
d Ondansetron 32 mg intravenously was used in the clinical trial. Although this dose was used in the trial, it is no longer the currently recommended dose. Refer to the ondansetron prescribing information for the current recommended dose.

14.2 Prevention of Nausea and Vomiting Associated with Emetogenic Chemotherapy, Including HEC in Pediatric Patients

One double-blind, active-controlled clinical trial was conducted in pediatric cancer patients. The total population (N = 327) had a mean age of 8.3 years (range two months to 16.9 years) and were 53% male; and 96% white. Patients were randomized and received a 20 mcg/kg (maximum 1.5 mg) intravenous infusion of palonosetron 30 minutes prior to the start of emetogenic chemotherapy (followed by placebo infusions four and eight hours after the dose of palonosetron) or 0.15 mg/kg of intravenous ondansetron 30 minutes prior to the start of emetogenic chemotherapy (followed by ondansetron 0.15 mg/kg infusions four and eight hours after the first dose of ondansetron, with a maximum total dose of 32 mg). Emetogenic chemotherapies administered included doxorubicin, cyclophosphamide (<1500 mg/m^2), ifosfamide, cisplatin, dactinomycin, carboplatin, and daunorubicin. Adjuvant corticosteroids, including dexamethasone, were administered with chemotherapy in 55% of patients.

Complete Response in the acute phase of the first cycle of chemotherapy was defined as no vomiting, no retching, and no rescue medication in the first 24 hours after starting chemotherapy. Efficacy was based on demonstrating non-inferiority of intravenous palonosetron compared to intravenous ondansetron. Non-inferiority criteria were met if the lower bound of the 97.5% confidence interval for the difference in Complete Response rates of intravenous palonosetron minus intravenous ondansetron was larger than -15%. The non-inferiority margin was 15%.

Efficacy Results

As shown in Table 8, intravenous palonosetron 20 mcg/kg (maximum 1.5 mg) demonstrated non-inferiority to the active comparator during the 0 to 24-hour time interval.

Table 8: Prevention of Acute Nausea and Vomiting (0 to 24 Hours) Associated with Emetogenic Chemotherapy in Pediatric Patients: Complete Response Rates
Palonosetron 20 mcg/kg intravenously (N=165) | Ondansetron 0.15 mg/kg for three intravenous doses (N=162) | Difference [97.5% Confidence Interval]a: Palonosetron minus intravenous Ondansetron Comparator
59.4% | 58.6% | 0.36% [-11.7%, 12.4%]
aTo adjust for multiplicity of treatment groups, a lower-bound of a 97.5% confidence interval was used to compare to -15%, the negative value of the non-inferiority margin.

In patients that received palonosetron at a lower dose than the recommended dose of 20 mcg/kg, non-inferiority criteria were not met.

14.3 Prevention of Postoperative Nausea and Vomiting in Adults

In a multicenter, randomized, stratified, double-blind, parallel-group, clinical trial, palonosetron was compared to placebo for PONV in 546 patients undergoing abdominal and gynecological surgery. All patients received general anesthesia. The trial was conducted predominantly in the US in the out-patient setting for patients undergoing elective gynecologic or abdominal laparoscopic surgery and stratified at randomization for the following risk factors: gender, non-smoking status, history of PONV and/or motion sickness.

Patients were randomized to receive a single dose of palonosetron 0.025 mg, 0.050 mg or 0.075 mg or placebo, each given intravenously immediately prior to induction of anesthesia. Antiemetic activity of was evaluated during the 0 to 72-hour time period after surgery.

Of the 138 patients treated with palonosetron 0.075 mg and evaluated for efficacy, 96% were women; 66% had a history of PONV or motion sickness; 85% were non-smokers. As for race, 63% were White, 20% were Black, 15% were Hispanic, and 1% were Asian. The age of patients ranged from 21 to 74 years, with a mean age of 38 years. Three patients were greater than 65 years of age.

Co-primary efficacy measures were Complete Response (CR) defined as no emetic episode and no use of rescue medication in 0 to 24 hours and 24 to 72 hours postoperatively.

Secondary efficacy endpoints included:

- Complete Response (CR) 0 to 48 hours and 0 to 72 hours
- Complete Control (CC) defined as CR and no more than mild nausea
- Severity of nausea (none, mild, moderate, severe)

The primary hypothesis was that at least one of the three palonosetron doses were superior to placebo.

Complete Response Rates for palonosetron 0.075 mg and placebo in this trial are described in the Table 9.

Table 9: Prevention of Postoperative Nausea and Vomiting in Adults: Complete Response Rates
Treatment | n/N (%) | Palonosetron vs Placebo
Treatment | n/N (%) | Δ | p-valuea
Co-primary Endpoints
Complete Response Rate (0 to 24 hours)
Palonosetron 0.075 mg intravenously | 59/138 (42.8%) | 16.8% | 0.004
Placebo | 35/135 (25.9%)
Complete Response Rate (24 to 72 hours)
Palonosetron 0.075 mg intravenously | 67/138 (48.6%) | 7.8% | 0.188
Placebo | 55/135 (40.7%)
a To reach statistical significance for each co-primary endpoint, the required significance limit for the lowest
p- value was p<0.017.
Δ Difference (%): palonosetron 0.075 mg minus placebo

Palonosetron as a single dose of 0.075 mg reduced the severity of nausea compared to placebo. Analyses of other secondary endpoints indicate that palonosetron 0.075 mg was numerically better than placebo, however, statistical significance was not formally demonstrated.

A randomized, double-blind, multicenter, placebo-controlled, dose ranging study was performed to evaluate palonosetron for PONV following abdominal or vaginal hysterectomy. Five intravenous doses (0.1, 0.3, 1.0, 3.0 and 30 mcg/kg) were evaluated in a total of 381 intent-to-treat patients. The primary efficacy measure was the proportion of patients with CR in the first 24 hours after recovery from surgery. The lowest effective dose of palonosetron was 1 mcg/kg (approximately 0.075 mg) which had a CR rate of 44% versus 19% for placebo, p=0.004 and significantly reduced the severity of nausea versus placebo, p=0.009.

16 HOW SUPPLIED/STORAGE AND HANDLING

POSFREATM injection is supplied as a sterile, clear and colorless solution in single-dose vials as follows:

NDC Number | Strength | Package
83831-105-01 | 0.25 mg palonosetron in 5 mL (0.05 mg/mL) | 1 vial/carton
83831-104-05 | 0.075 mg palonosetron in 1.5 mL (0.05 mg/mL) | 5 vials/carton

Storage

- Store at 20°C to 25°C (68°F to 77°F); [Excursions permitted to 15°C to 30°C (59°F to 86°F)].
- Protect from freezing.
- Protect from light.

17 PATIENT COUNSELING INFORMATION

Advise the patient or caregiver to read the FDA-approved patient labeling (Patient Information).

Hypersensitivity Reactions

Advise patients that hypersensitivity reactions, including anaphylaxis and anaphylactic shock, have been reported in patients with or without known hypersensitivity to other 5-HT3 receptor antagonists. Advise patients to seek immediate medical attention if any signs or symptoms of a hypersensitivity reaction occur with administration of POSFREA [see Warnings and Precautions (5.1)].

Serotonin Syndrome

Advise patients of the possibility of serotonin syndrome, especially with concomitant use of POSFREA and another serotonergic agent such as medications to treat depression and migraines. Advise patients to seek immediate medical attention if the following symptoms occur: changes in mental status, autonomic instability, neuromuscular symptoms with or without gastrointestinal symptoms [see Warnings and Precautions (5.2)].

Manufactured for:

Avyxa Pharma, LLC

New Jersey 07054, USA

SPL PATIENT PACKAGE INSERT

PATIENT INFORMATION
POSFREATM (pos-FREE-uh) (palonosetron) injection,
for intravenous use

Read this Patient Information before you receive POSFREA and each time you receive POSFREA. There may be new information. This information does not take the place of talking with your doctor about your medical condition or your treatment.

What is POSFREA?
POSFREA is a prescription medicine called an "antiemetic."
POSFREA is used in adults to help prevent the nausea and vomiting that happens:
● right away or later with certain anti-cancer medicines (chemotherapy)
● up to 24 hours while recovering from anesthesia after surgery
POSFREA is used in children 1 month old to less than 17 years of age to help prevent the nausea and vomiting that happens right away with certain anti-cancer medicines (chemotherapy).
● It is not known if POSFREA is safe and effective in children less than 1 month old to help prevent nausea and vomiting after chemotherapy.
● It is not known if POSFREA is safe and effective in children for the prevention of nausea and vomiting while recovering from anesthesia after surgery.

Who should not receive POSFREA?
Do not receive POSFREA if you are allergic to palonosetron hydrochloride or any of the ingredients in POSFREA. See the end of this leaflet for a complete list of ingredients in POSFREA.

What should I tell my doctor before receiving POSFREA?
Before receiving POSFREA, tell your doctor about all of your medical conditions, including if you:
● have had an allergic reaction to another medicine for nausea or vomiting
● are pregnant or plan to become pregnant. It is not known if POSFREA will harm your unborn baby.
● are breastfeeding or plan to breastfeed. It is not known if POSFREA passes into your breast milk or if it will affect your baby or your breast milk. Talk to your doctor about the best way to feed your baby if you will receive POSFREA.
Tell your doctor about all of the medicines you take, including prescription and over-the-counter medicines, vitamins and herbal supplements.
POSFREA and certain other medicines can affect each other, causing serious side effects.

How will I receive POSFREA?
● POSFREA will be given to you in your vein by intravenous (I.V.) injection.
● POSFREA is usually given about 30 minutes before you receive your anti- cancer medicine (chemotherapy) or right before anesthesia for surgery.

What are the possible side effects of POSFREA? POSFREA may cause serious side effects, including:
● Serious allergic reactions , such as anaphylaxis. Get emergency medical help right away if you get any of the following symptoms.
○ hives
○ swollen face
○ breathing trouble
○ chest pain
● Serotonin Syndrome. A possible life threatening problem called serotonin syndrome can happen with medicines called 5-HT3 receptor antagonists, including POSFREA, especially when used with medicines used to treat depression and migraine headaches called serotonin reuptake inhibitors (SSRIs), serotonin and norepinephrine reuptake inhibitors (SNRIs), monoamine oxidase inhibitors (MAOIs) and certain other medicines. Tell your doctor or nurse right away if you have any of the following symptoms of serotonin syndrome:
○ agitation, seeing things that are not there (hallucinations), confusion, or coma
○ fast heartbeat or unusual and frequent changes in your blood pressure
○ dizziness, sweating, flushing, or fever
○ tremors, stiff muscles, muscle twitching, overactive reflexes, or loss of coordination
○ seizures
○ nausea, vomiting, or diarrhea
The most common side effects in adults who receive POSFREA to help prevent nausea and vomiting that happens with certain anti-cancer medicine (chemotherapy) include: headache and constipation.
The most common side effects in adults who receive POSFREA to help prevent nausea and vomiting that happens while recovering from anesthesia after surgery include: serious or life-threatening heart rhythm changes (QT prolongation), slow heartbeat, headache, and constipation.
These are not all the possible side effects of POSFREA.
Call your doctor for medical advice about side effects. You may report side effects to FDA at 1-800-FDA-1088.

General information about the safe and effective use of POSFREA.
Medicines are sometimes prescribed for purposes other than those listed in a Patient Information leaflet. You can ask your doctor or pharmacist for information about POSFREA that is written for health professionals.

What are the ingredients in POSFREA?
Active ingredient: palonosetron hydrochloride
Inactive ingredients: mannitol and sodium acetate trihydrate in water for intravenous administration.
Hydrochloric acid or sodium hydroxide may have been added to adjust pH.
Rx Only

Manufactured for:
Avyxa Pharma, LLC
New Jersey 07054, USA
For more information call 1-888-520-0954.
Made in India

This Patient Information has been approved by the U.S. Food and Drug Administration. Revised: 04/2025

PACKAGE LABEL.PRINCIPAL DISPLAY PANEL

Posfrea (palonosetron) Injection, 0.25mg/5 mL -Container label
Posfrea (palonosetron) Injection, 0.25mg/5 mL -Carton label